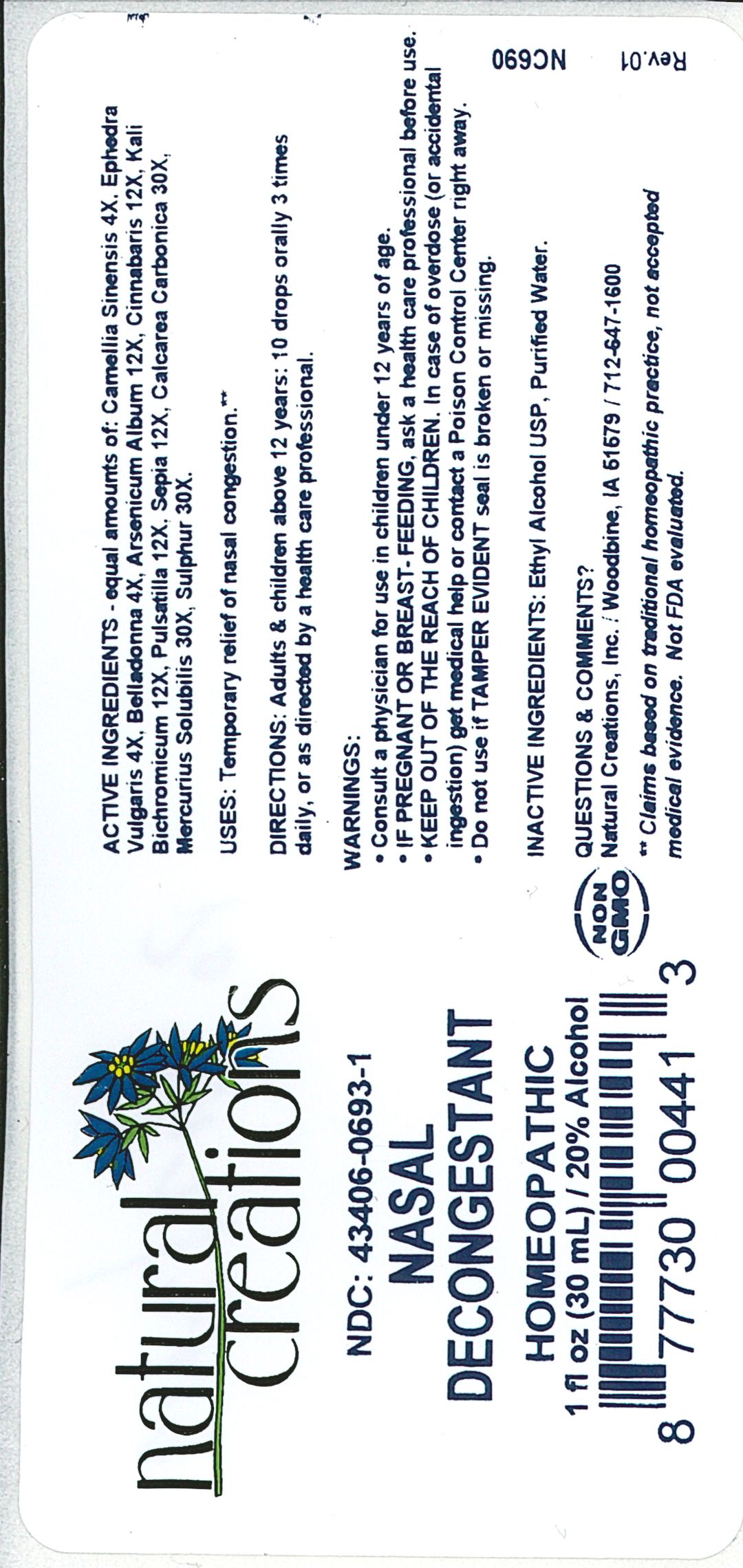 DRUG LABEL: Nasal Decongestant
NDC: 43406-0693 | Form: LIQUID
Manufacturer: Natural Creations, Inc
Category: homeopathic | Type: HUMAN OTC DRUG LABEL
Date: 20181221

ACTIVE INGREDIENTS: CAMELLIA SINENSIS WHOLE 4 [hp_X]/1 mL; EPHEDRA DISTACHYA FLOWERING TWIG 4 [hp_X]/1 mL; ATROPA BELLADONNA 4 [hp_X]/1 mL; ARSENIC TRIOXIDE 12 [hp_X]/1 mL; MERCURIC SULFIDE 12 [hp_X]/1 mL; POTASSIUM DICHROMATE 12 [hp_X]/1 mL; PULSATILLA VULGARIS WHOLE 12 [hp_X]/1 mL; SEPIA OFFICINALIS JUICE 12 [hp_X]/1 mL; OYSTER SHELL CALCIUM CARBONATE, CRUDE 30 [hp_X]/1 mL; MERCURIUS SOLUBILIS 30 [hp_X]/1 mL; SULFUR 30 [hp_X]/1 mL
INACTIVE INGREDIENTS: ALCOHOL; WATER

Nasal Decongestant

ACTIVE INGREDIENT

ACTIVE INGREDIENTS - equal amounts of: Camellia Sinensis 4X, Ephedra Vulgaris 4X, Belladonna 4X, Arsenicum Album 12X, Cinnabaris 12X, Kali Bichromicum 12X, Pulsatilla 12X, Sepia 12X, Calcarea Carbonica 30X, Mercurius Solubilis 30X, Sulphur 30X

INDICATIONS AND USAGE

USES: Temporary relief of nasal congestion.**

PURPOSE

USES: Temporary relief of nasal congestion.**

DOSAGE AND ADMINISTRATION

DIRECTIONS: Adults & children above 12 years: 10 drops orally 3 times daily, or as directed by a health care professional.

KEEP OUT OF REACH OF CHILDREN

KEEP OUT OF THE REACH OF CHILDREN. In case of overdose (or accidental ingestion) get medical help or contact a Poison Control Center right away.

WARNINGS:

- Consult a physician for use in children under 12 years of age.
- IF PREGNANT OR BREAST-FEEDING, ask a health care professional before use.
- KEEP OUT OF THE REACH OF CHILDREN. In case of overdose (or accidental ingestion) get medical help or contact a Poison Control Center right away.
- Do not use if TAMPER EVIDENT seal is broken or missing.

INACTIVE INGREDIENTS: Ethyl Alcohol USP, Purified Water

QUESTIONS & COMMENTS?

Natural Creations, Inc. / Woodbine, IA 51579 / 712-647-1600

REFERENCES

**Claims based on traditional homeopathic practice, not accepted medical evidence. Not FDA evaluated.

PACKAGE LABEL

NDC:43406-0693-1

Nasal Decongestant

HOMEOPATHIC

1 fl oz (30mL) / 20% Alcohol